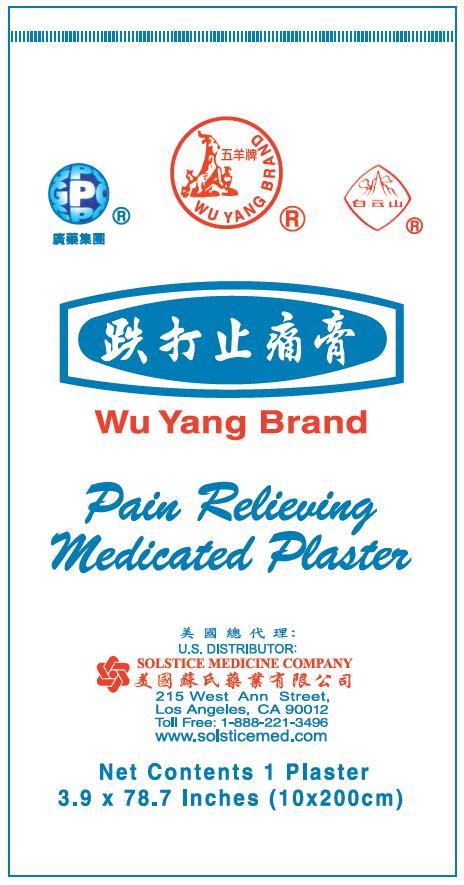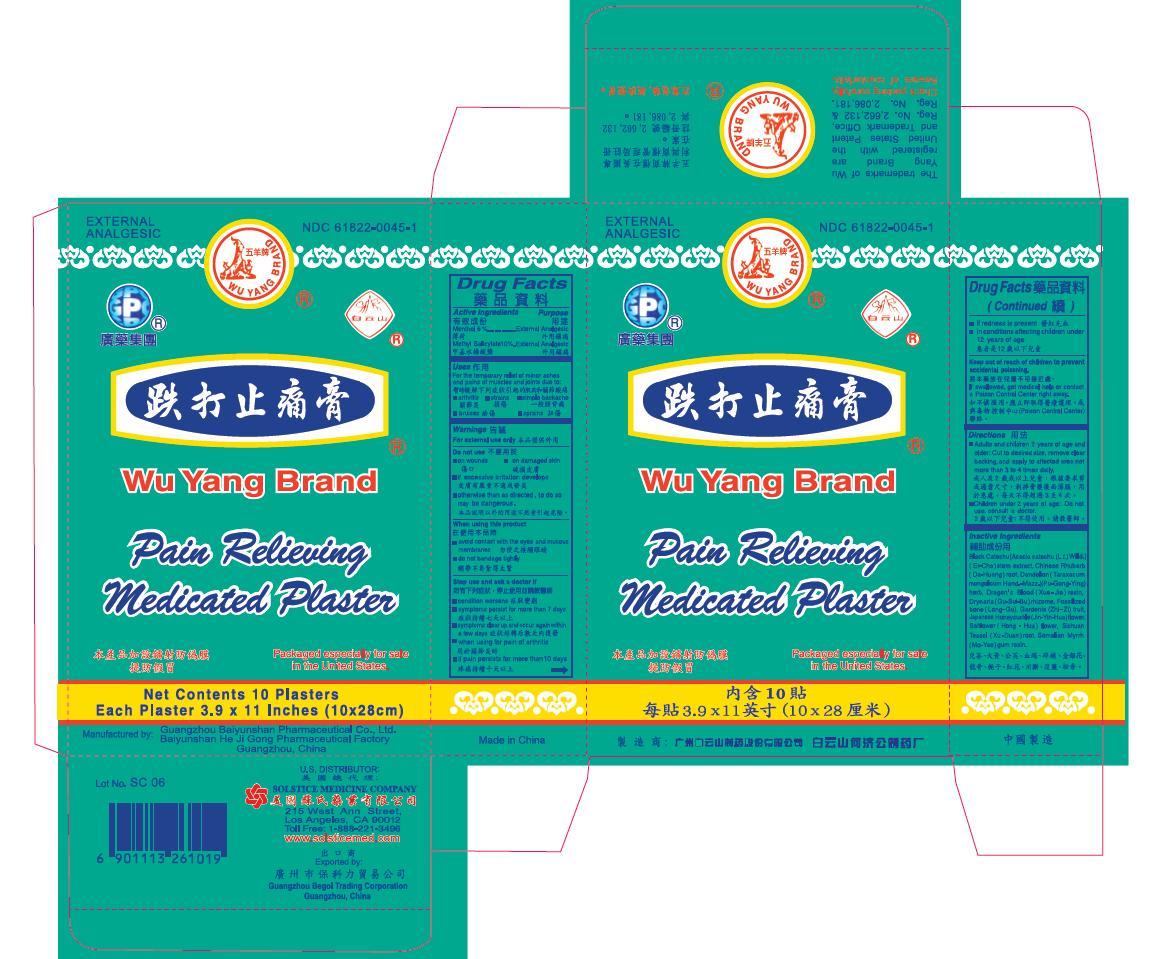 DRUG LABEL: WU YANG BRAND MEDICATED
NDC: 61822-0045 | Form: PLASTER
Manufacturer: GUANGZHOU BAIYUNSHAN PHARMACEUTICAL CO., LTD. BAIYUNSHAN HEJIGONG PHARMACEUTICAL FACTORY
Category: otc | Type: HUMAN OTC DRUG LABEL
Date: 20191113

ACTIVE INGREDIENTS: MENTHOL 6 g/1 1; METHYL SALICYLATE 10 g/1 1
INACTIVE INGREDIENTS: BLACK CATECHU; POLYGONUM CUSPIDATUM WHOLE; TARAXACUM MONGOLICUM; DAEMONOROPS DRACO RESIN; DRYNARIA FORTUNEI ROOT; MAMMAL BONE, FOSSILIZED; GARDENIA JASMINOIDES FRUIT; LONICERA JAPONICA FLOWER; SAFFLOWER; DIPSACUS ASPER ROOT; MYRRH

Drug Facts

Active ingredients
Menthol 6%
Methyl salicylate 10%

Purpose
External analgesic
External analgesic

Uses
For the temporary relief of minor aches and pains of muscles and joints due to:
simple backache
arthritis
strains
bruises
sprains

Warnings
For external use only

Do not use
on wounds
on damaged or irritated skin
if excessive irritation develops
otherwise than as directed. To do so may be dangerous.

When using this product
avoid contact with the eyes or mucous membranes
do not bandage tightly

Stop use and ask a doctor if
condition worsens
symptoms persist for more than 7 days
symptoms clear up and occur again within a few days
when using for pain of arthritis:
if pain persists for more than 10 days
if redness is present
in conditions affecting children under 12 years of age

Keep out of reach of children to avoid accidental poisoning.
If swallowed, get medical help or contact a Poison Control Center right away.

Directions
Adults and children 2 years of age and older: Cut to desired size, remove clear backing, and apply to affected area not more than 3 to 4 times daily.
Children under 2 years of age: Do not use, consult a doctor.

Other information
keep in a tightly closed container
store at room temperature 15º to 30º C (59º to 86º F), away from sunlight

Questions or comments? (888) 221-3496 M-F 9 am to 5 pm
you may also report serious side effects to this phone number

PACKAGE LABEL

WU YANG BRAND MEDICATED PLASTER

NDC 61822-0045-1

External Analgesic

10 Plasters – 3.9 x 11 inches (10 x 28 cm) each

WU YANG BRAND MEDICATED PLASTER

NDC 61822-0045-2

External Analgesic

1 Plaster – 3.9 x 78.7 inches (10 x 200 cm)